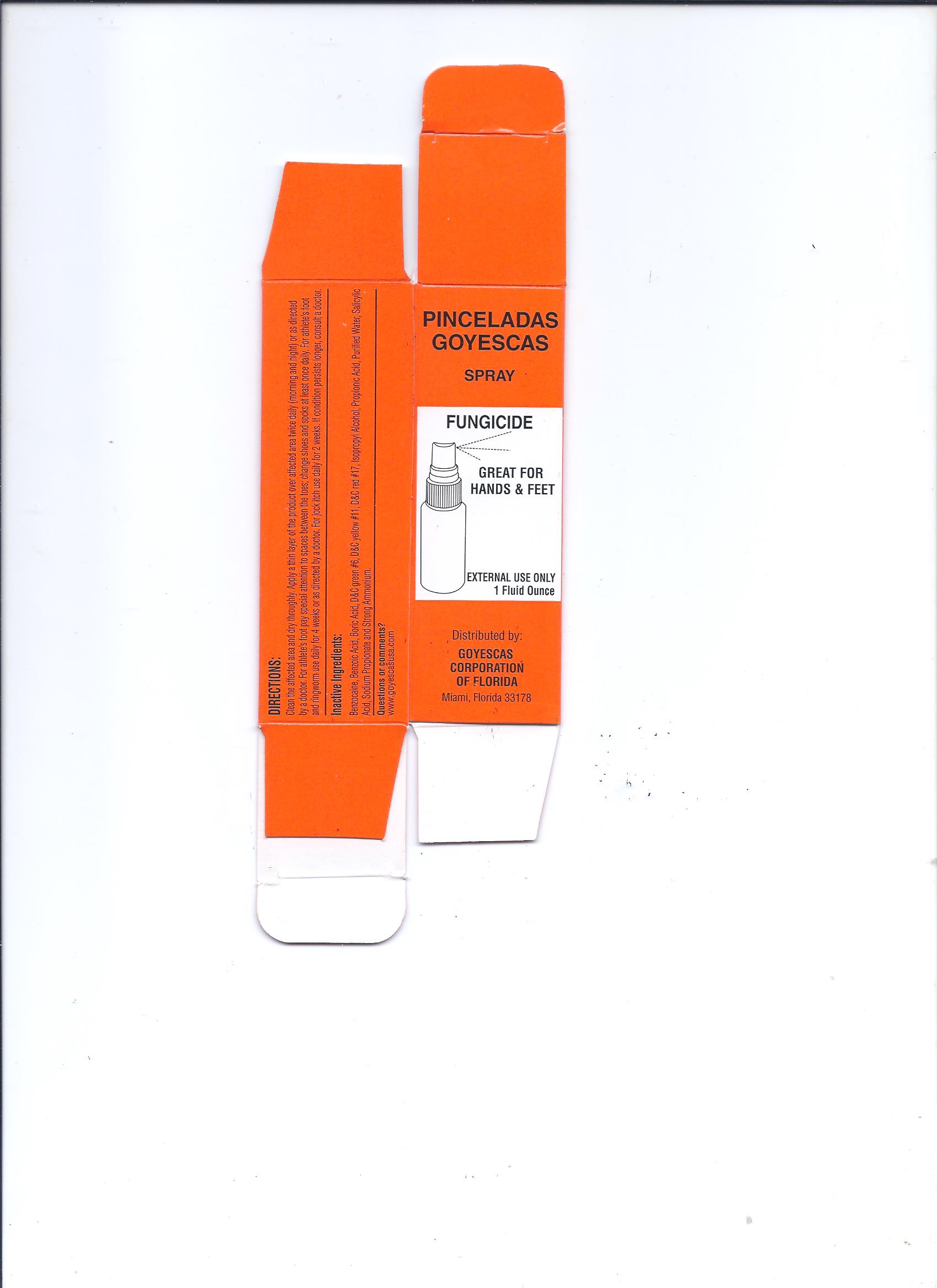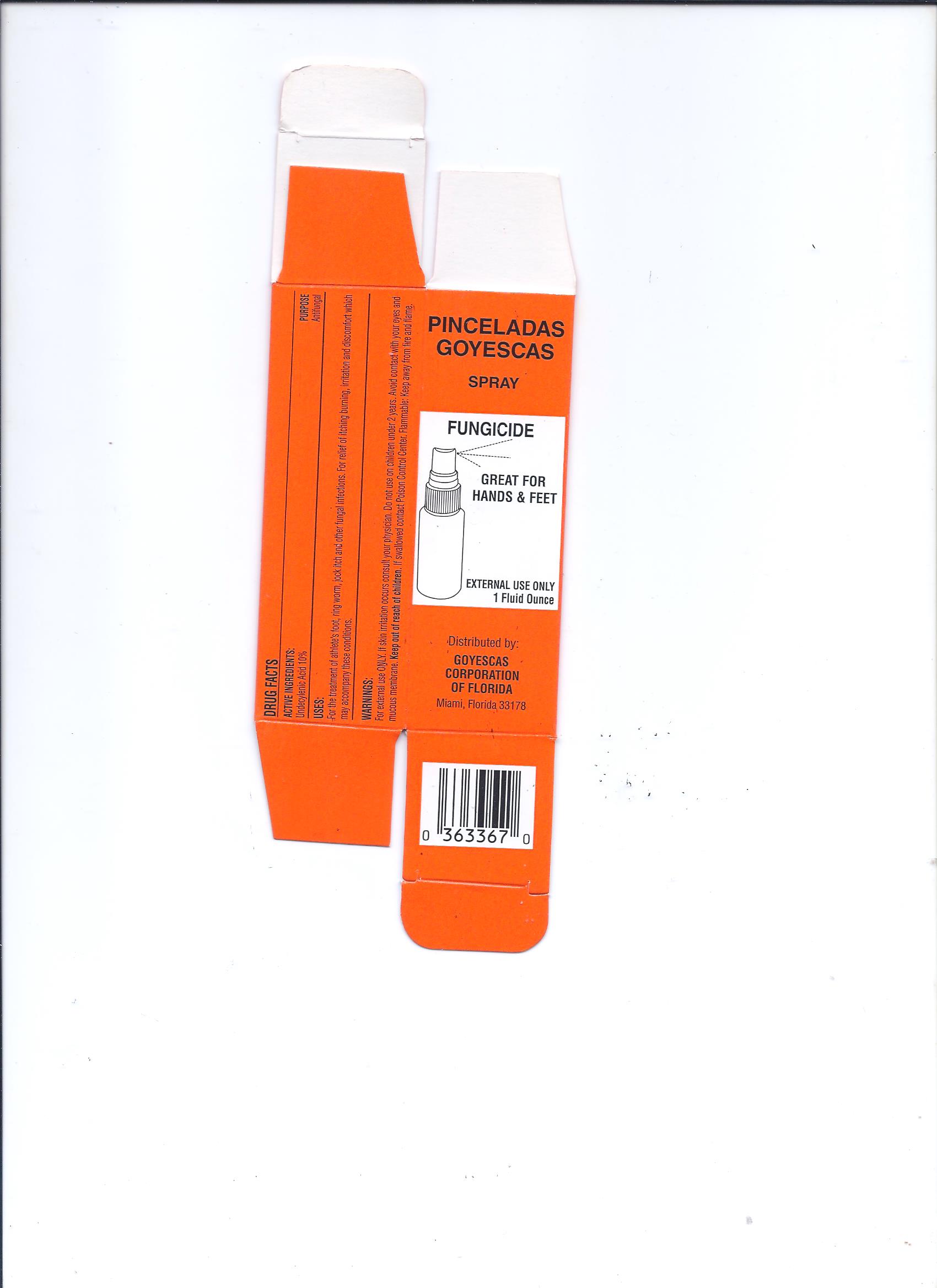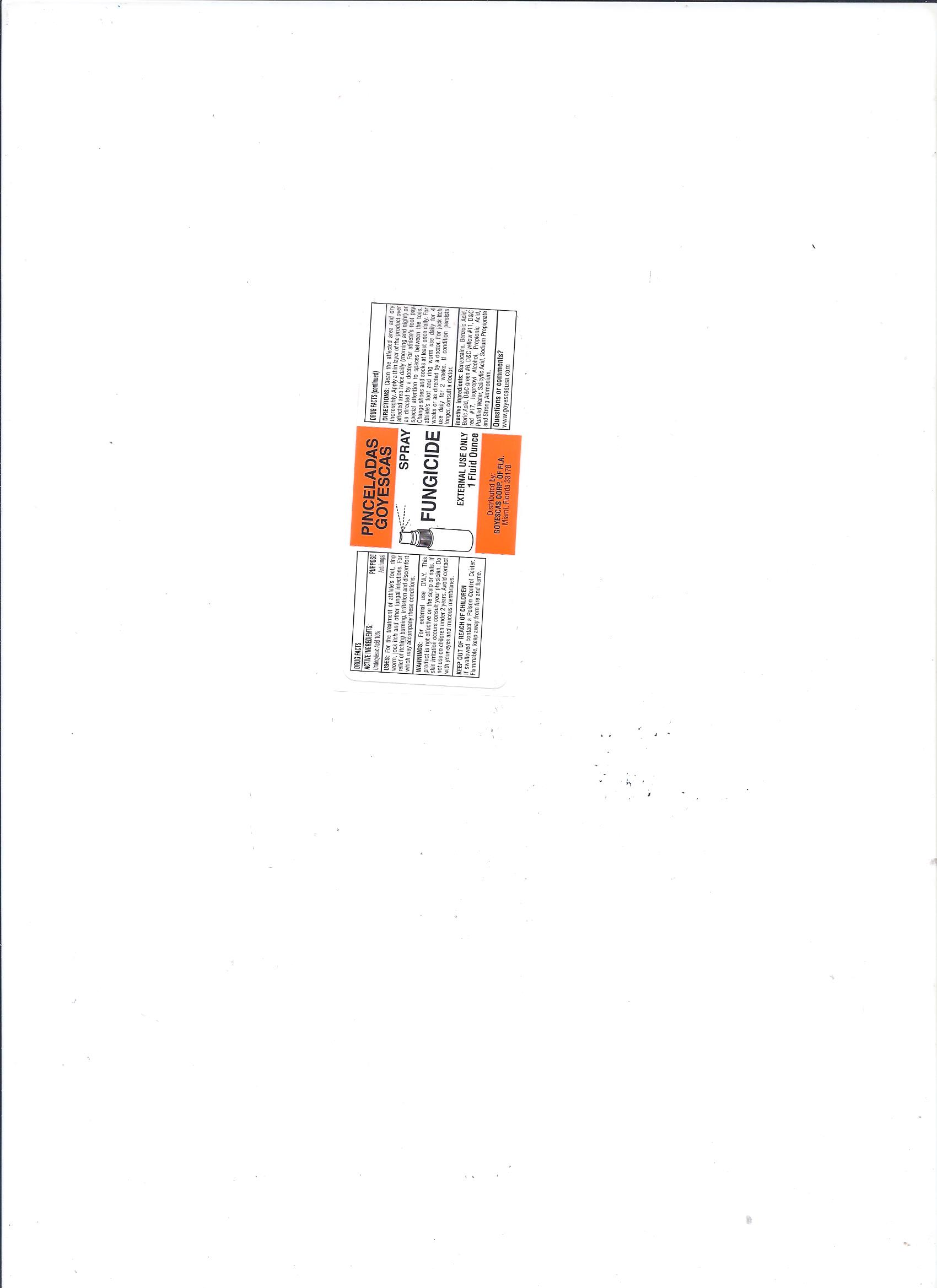 DRUG LABEL: Pinceladas Goyescas Original
NDC: 11856-3367 | Form: LIQUID
Manufacturer: GOYESCAS OF FLA
Category: otc | Type: HUMAN OTC DRUG LABEL
Date: 20151019

ACTIVE INGREDIENTS: UNDECYLENIC ACID 100 mg/1 mL
INACTIVE INGREDIENTS: SALICYLIC ACID; SODIUM PROPIONATE; D&C RED NO. 17; PROPIONIC ACID; WATER; BENZOCAINE; 2,3-DIHYDROXY BENZOIC ACID; BORIC ACID; D&C GREEN NO. 6; D&C YELLOW NO. 11; ISOPROPYL ALCOHOL

Warnings

For external use ONLY. If irritation occurs consult your physician. Do not use on children under 2 years. Avoid contact with your eyes and mucous membrane. Keep out of reach of children. If swallowed contact Poison Control Center. Flammable: Keep away from fire and flame.

Inactive Ingredients

Benzocaine, Benzoic Acid, Boric Acid, D&C green #6, D&C yellow #11, D&C red #17, Isopropyl Alcohol, Propionic Acid, Purified Water, Salicylic Acid, Sodium Propionate and Strong Ammonium.

Uses

For the treatment of athletes foot, jock itch and other fungal infections. For relief of itching burning irritation and discomfort which may accompany these conditions.

Purpose

DRUG FACTS: PURPOSE

Undecylenic Acid 10% Antifungal

Warnings

For external use ONLY. If irritation occurs consult your physician. Do not use on children under 2 years. Avoid contact with your eyes and mucous membrane. Keep out of reach of children. If swallowed contact Poison Control Center. Flammable: Keep away from fire and flame.

Active Ingredients

DRUG FACTS:

ACTIVE INGREDIENTS: PURPOSE

Undecylenic Acid 10% Antifungal

Directions

Clean the affected area and dry thoroughly. Apply a thin layer of product over affected area twice daily (morning and night) or as directed by a doctor. For athlete’s foot pay special attention to spaces between the toes; change shoes and socks at least at least once daily. For athletes and ring worm use daily for 4 weeks or as directed by a doctor. For jock itch use daily for 2 weeks. If condition persists longer consult a doctor.

DRUG FACTS:

ACTIVE INGREDIENTS: PURPOSE

Undecylenic Acid 10% Antifungal

USES:

For the treatment of athletes foot, jock itch and other fungal infections. For relief of itching burning irritation and discomfort which may accompany these conditions.

WARNINGS:

For external use ONLY. If irritation occurs consult your physician. Do not use on children under 2 years. Avoid contact with your eyes and mucous membrane. Keep out of reach of children. If swallowed contact Poison Control Center. Flammable: Keep away from fire and flame.

DIRECTIONS:

Clean the affected area and dry thoroughly. Apply a thin layer of product over affected area twice daily (morning and night) or as directed by a doctor. For athlete’s foot pay special attention to spaces between the toes; change shoes and socks at least at least once daily. For athletes and ring worm use daily for 4 weeks or as directed by a doctor. For jock itch use daily for 2 weeks. If condition persists longer consult a doctor.

Inactive Ingredients:

Benzocaine, Benzoic Acid, Boric Acid, D&C green #6, D&C yellow #11, D&C red #17, Isopropyl Alcohol, Propionic Acid, Purified Water, Salicylic Acid, Sodium Propionate and Strong Ammonium.